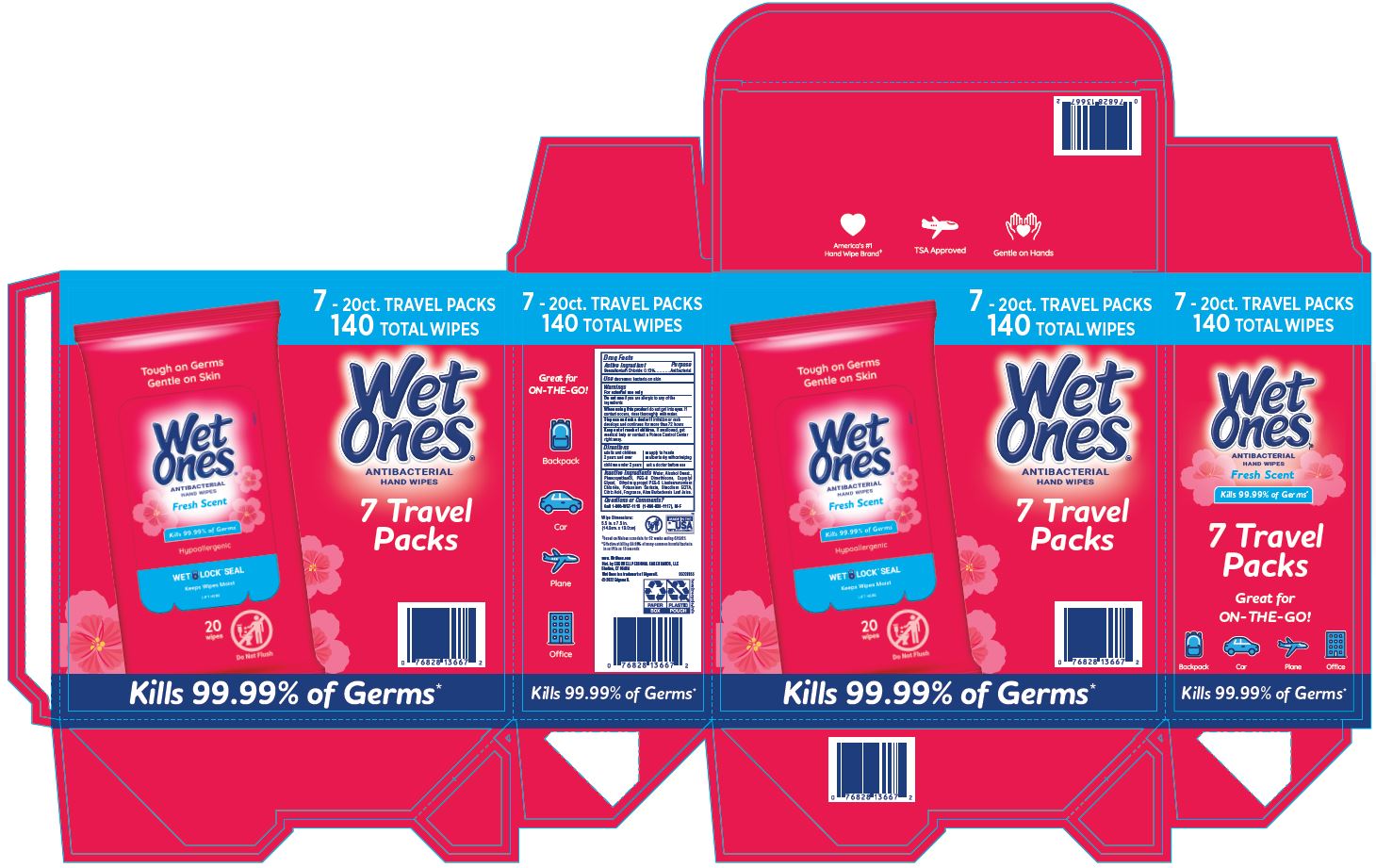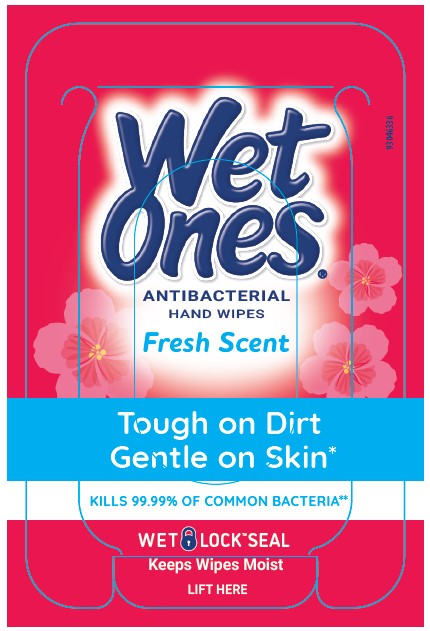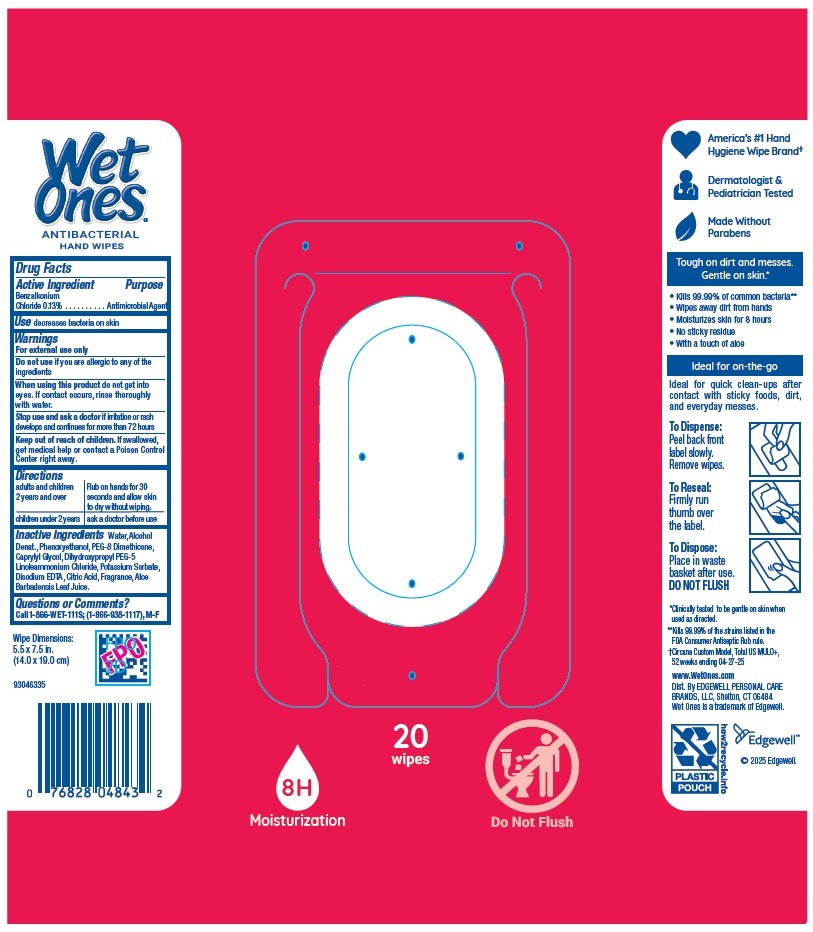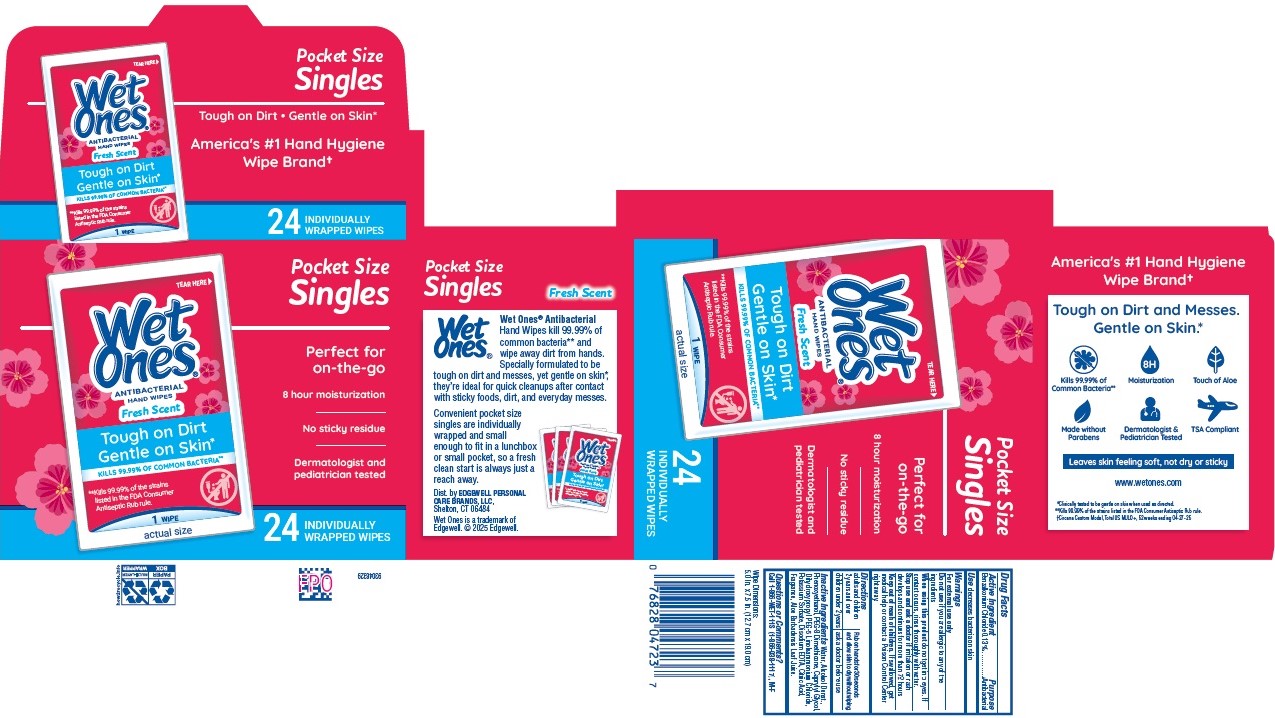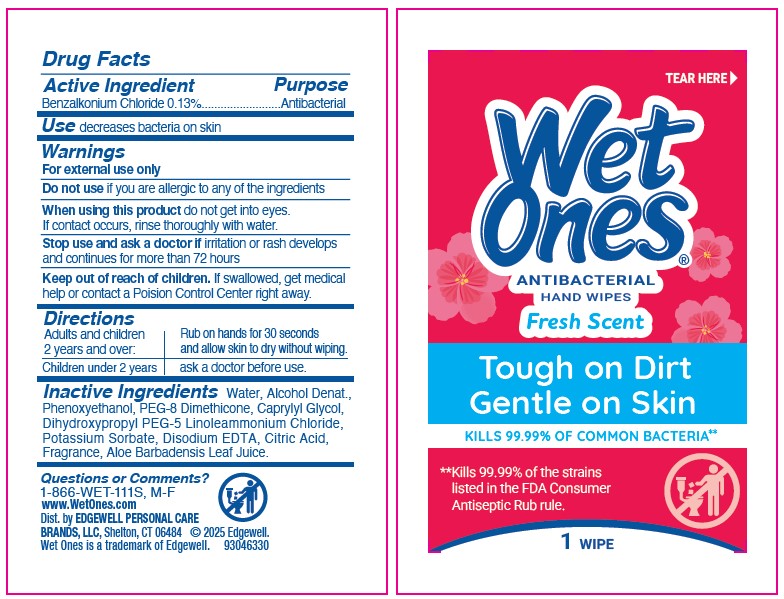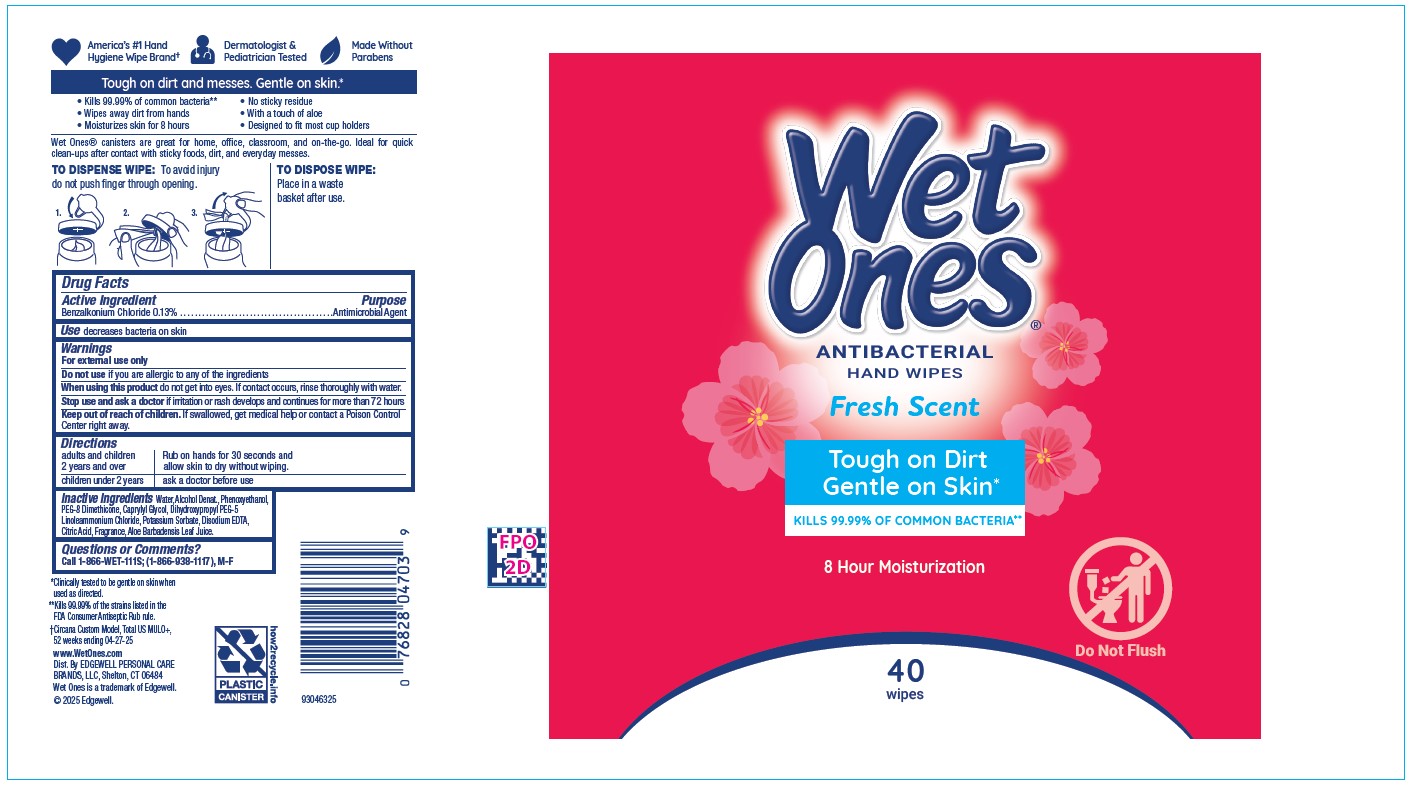 DRUG LABEL: WET ONES
NDC: 63354-774 | Form: SWAB
Manufacturer: Edgewell Personal Care Brands LLC
Category: otc | Type: HUMAN OTC DRUG LABEL
Date: 20250917

ACTIVE INGREDIENTS: BENZALKONIUM CHLORIDE 0.13 g/1 1
INACTIVE INGREDIENTS: WATER; CAPRYLYL GLYCOL; PEG-8 DIMETHICONE; EDETATE DISODIUM; CITRIC ACID MONOHYDRATE; PHENOXYETHANOL; DIHYDROXYPROPYL PEG-5 LINOLEAMMONIUM CHLORIDE; POTASSIUM SORBATE; ALOE VERA LEAF; ALCOHOL

Active Ingredient

Benzalkonium Chloride 0.13%

Purpose

Antimicrobial Agent

Use

decreases bacteria on skin

Warnings

For external use only

Do not use

if you are allergic to any of the ingredients

When using this product

do not get into eyes. If contact occurs, rinse thoroughly with water.

Stop use and ask a doctor

if irritation or rash develops and continues for more than 72 hours

Keep out of reach of children.

If swallowed, get medical help or contact a Poison Control Center right away.

Directions

adults and children 2 years and over | Rub on hands for 30 seconds and allow skin to dry without wiping.

children under 2 years | ask a doctor before use

Inactive Ingredients

Water, Alcohol Denat., Phenoxyethanol, PEG-8 Dimethicone, Caprylyl Glycol, Dihydroxypropyl PEG-5 Linoleammonium Chloride, Potassium Sorbate, Disodium EDTA, Citric Acid, Fragrance, Aloe Barbadensis Leaf Juice.

Questions or Comments?

Call 1-866-WET-111S; (1-866-938-1117), M-F

Principal Display Panel

Wet

Ones

ANTIBACTERIAL

HAND WIPE

Fresh Scent

Tough On Dirt

Gentle on Skin

KILLS 99.99% OF COMMON BACTERIA

WET LOCK SEAL

Keeps Wipes Moist

LIFT HERE

8H Moisturization

20

wipes

Do Not Flush

TEAR HERE

Wet

Ones

ANTIBACTERIAL

HAND WIPE

Fresh Scent

Tough On Dirt

Gentle on Skin

KILLS 99.99% OF COMMON BACTERIA**

**Kills 99.99% of the strains

listed in the FDA Consumer

Antiseptic Rub rule.

1 WIPE

TEAR HERE

Wet

Ones

ANTIBACTERIAL

HAND WIPE

Fresh Scent

Tough On Dirt

Gentle on Skin

KILLS 99.99% OF COMMON BACTERIA**

**Kills 99.99% of the strains

listed in the FDA Consumer

Antiseptic Rub rule.

1 WIPE

actual size

Pocket Size

Singles

Perfect for

on-the-go

8 hour moisturization

No sticky residue

Dermatologist and

pediatrician tested

24 INDIVIDUALLY

WRAPPED WIPES

Wet

Ones

ANTIBACTERIAL

HAND WIPE

Fresh Scent

Tough On Dirt

Gentle on Skin

KILLS 99.99% OF COMMON BACTERIA

8 Hour Moisturization

Do Not Flush

40

wipes

7 - 20ct. TRAVEL PACKS
140 TOTAL WIPES
Wet
Ones
ANTIBACTERIAL
HAND WIPE
7 Travel
Packs
Kills 99.99% of Germs*